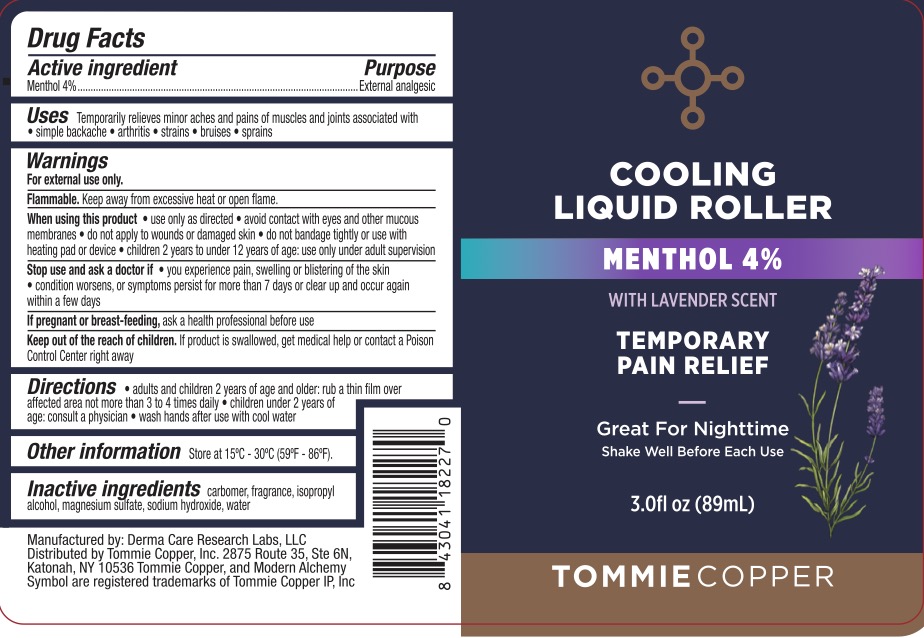 DRUG LABEL: Tommie Copper Cooling Roller Lavender Scent
NDC: 72562-185 | Form: GEL
Manufacturer: Tommie Copper, Inc.
Category: otc | Type: HUMAN OTC DRUG LABEL
Date: 20260226

ACTIVE INGREDIENTS: MENTHOL, (+)- 4 g/100 mL
INACTIVE INGREDIENTS: CARBOMER 940; WATER; SODIUM HYDROXIDE; ISOPROPYL ALCOHOL; MAGNESIUM SULFATE, UNSPECIFIED

Tommie Copper Cooling Liquid Roller, Menthol 4%

ACTIVE INGREDIENT

Menthol 4%

PURPOSE

External Analgesic

INDICATIONS AND USAGE

Temporarily relieves minor aches and pains of muscles and joints associated with simple backache, arthritis, strains, bruises, and sprains.

WARNINGS

For external use only.

Flammable. Keep away from excessive heat or open flame.

When using this product use only as directed. Avoid contact with eyes and mucous membranes, do not apply to wounds or damaged skin, do no apply to irritated skin or if excessive irritation develops, do not bandage tightly or use with heating pad or device. Children 12 years of age and older: use only under adult supervision.

Stop use and ask a doctor if you experience pain, swelling, or blistering of the skin, condition worsens, symptoms last more than 7 days or clear up and occur again within a few days.

PREGNANCY OR BREAST FEEDING

Ask a health professional before use.

KEEP OUT OF REACH OF CHILDREN

If product is swallowed, get medical help or contact a Poison Control Center right away.

DOSAGE AND ADMINISTRATION

Adults and children 2 years of age and older: rub a thin film over affected area not more than 3 to 4 times daily. Children under 2 years of age: consult a physician. Wash hands after use with cool water.

INACTIVE INGREDIENT

Carbomer, fragrance, isopropyl alcohol, magnesium sulfate, sodium hydroxide, water.